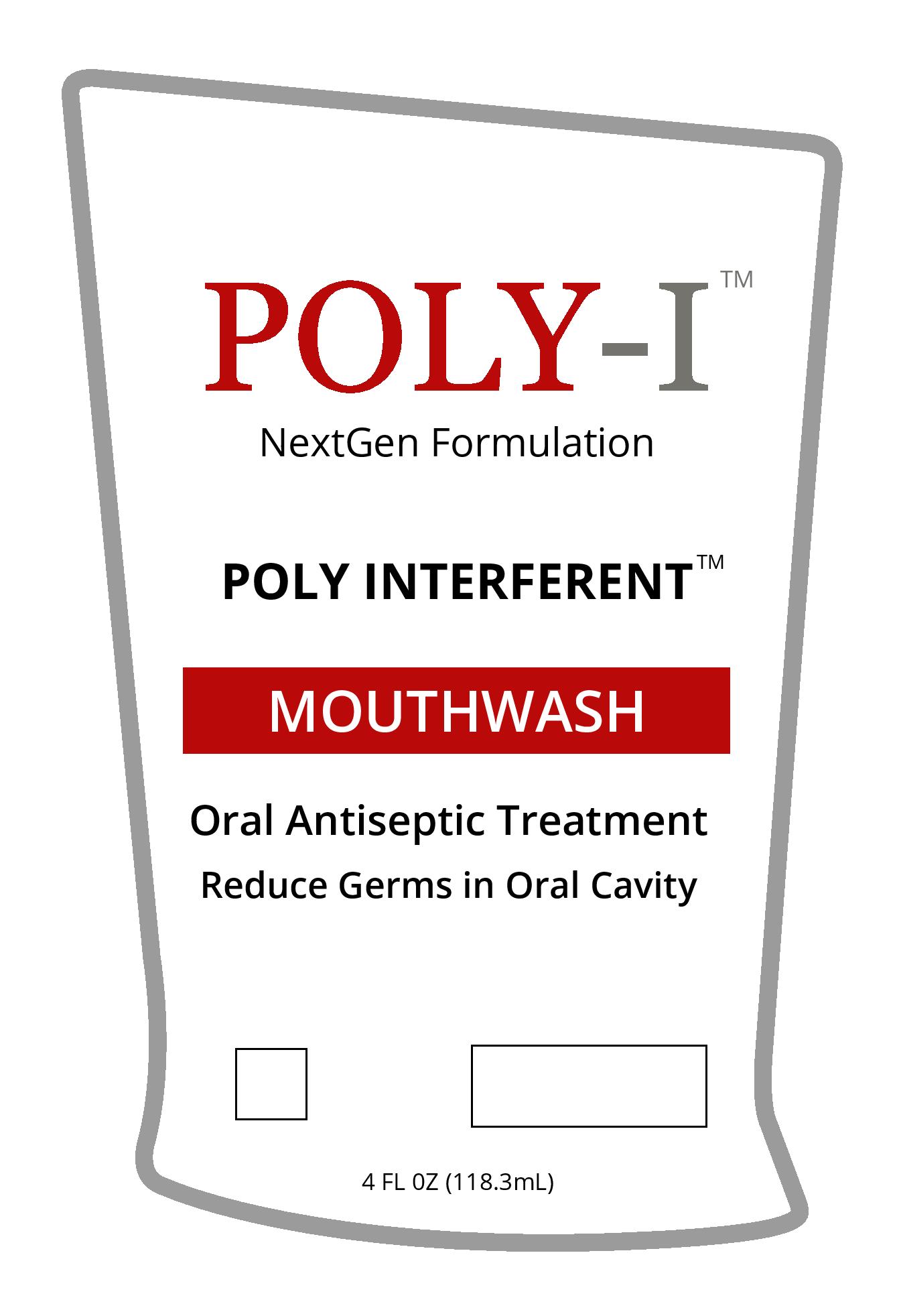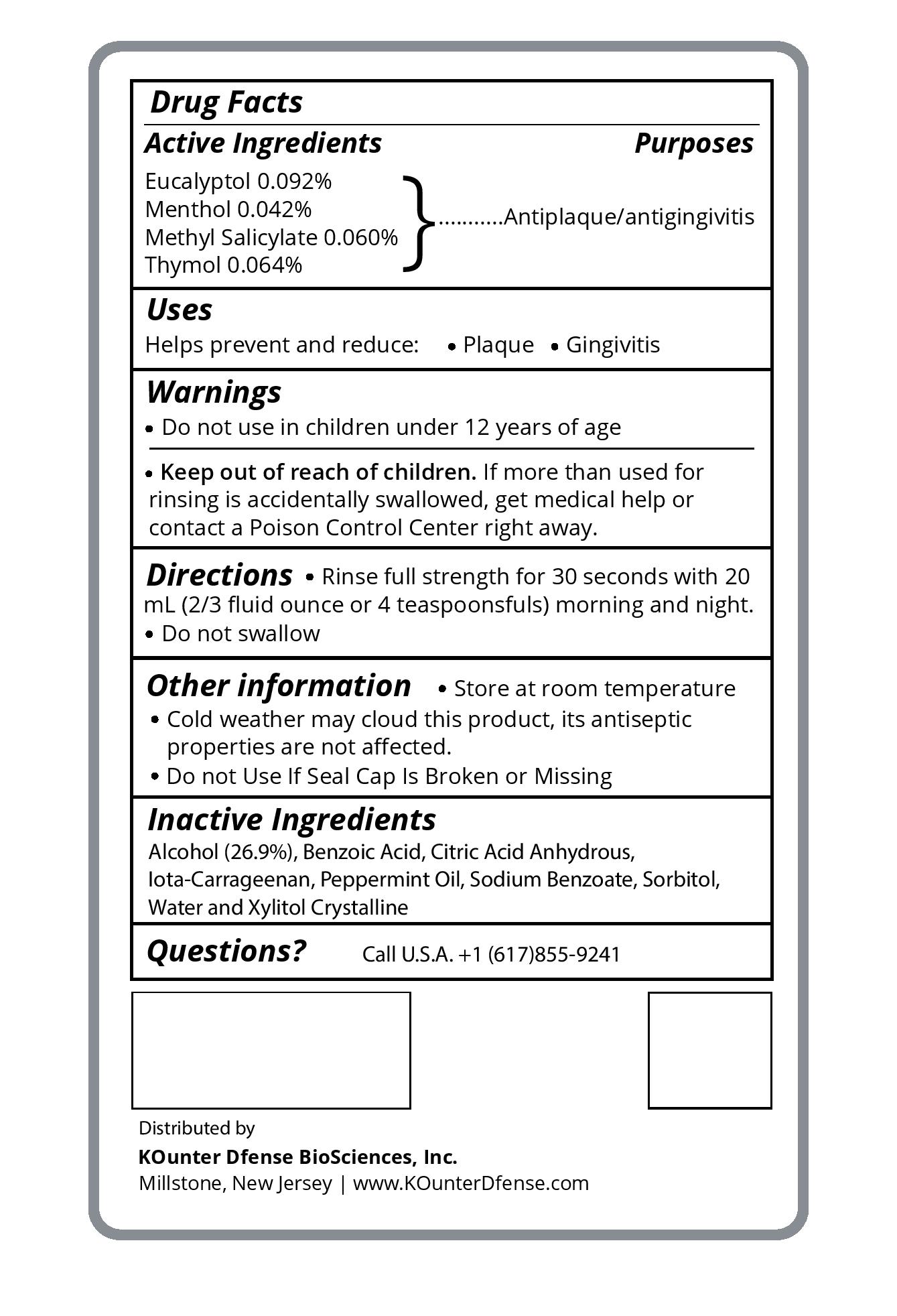 DRUG LABEL: Poly Interferent Mouthwas
NDC: 82005-322 | Form: MOUTHWASH
Manufacturer: KOunter Dfense BioSciences, Inc.
Category: otc | Type: HUMAN OTC DRUG LABEL
Date: 20211031

ACTIVE INGREDIENTS: METHYL SALICYLATE 0.6 mg/1 mL; THYMOL 0.64 mg/1 mL; EUCALYPTOL 0.92 mg/1 mL; MENTHOL, UNSPECIFIED FORM 0.42 mg/1 mL
INACTIVE INGREDIENTS: .IOTA.-CARRAGEENAN; PEPPERMINT OIL; SODIUM BENZOATE; WATER; XYLITOL; BENZOIC ACID; ANHYDROUS CITRIC ACID; SORBITOL; ALCOHOL

Poly-I NextGen Formulation
Poly Interferent Mouthwash

Active Ingredients

Eucalyptol 0.092%
Menthol 0.042%
Methyl Salicylate 0.060%
Thymol 0.064%

Purposes

Antiplaque/Antigingivitis

Uses

Helps Prevent and Reduce

- Plaque
- Gingivitis

Warnings

Do not use in children under 12 years of age.

Keep out of reach of children.

If more than used for rinsing is accidentally swallowed, get medical help or contact a Poison Control Center right away.

Keep Out of Reach of Children

Directions

Rinse full strength for 30 seconds with 20 mL (2/3 fluid ounce or 4 teaspoonsfuls) morning and night.

Do not swallow

Inactive Ingredients

Alcohol (26.9%), Benzoic Acid, Citric Acid Anhydrous, Iota-Carrageenan, Peppermint Oil, Sodium Benzoate, Sorbitol, Water and Xylitol Crystalline

Other Information

- Store at room temperature
- Cold weather may cloud this product, its antiseptic properties are not affected.
- Do not Use If Seal Cap Is Broken or Missing